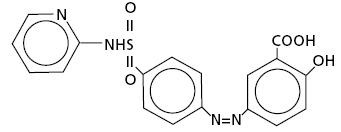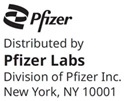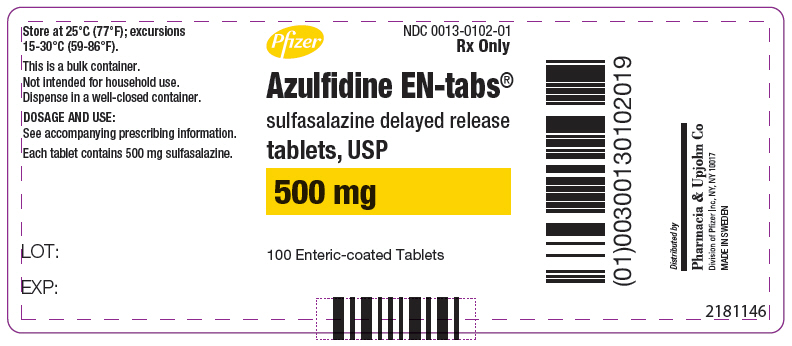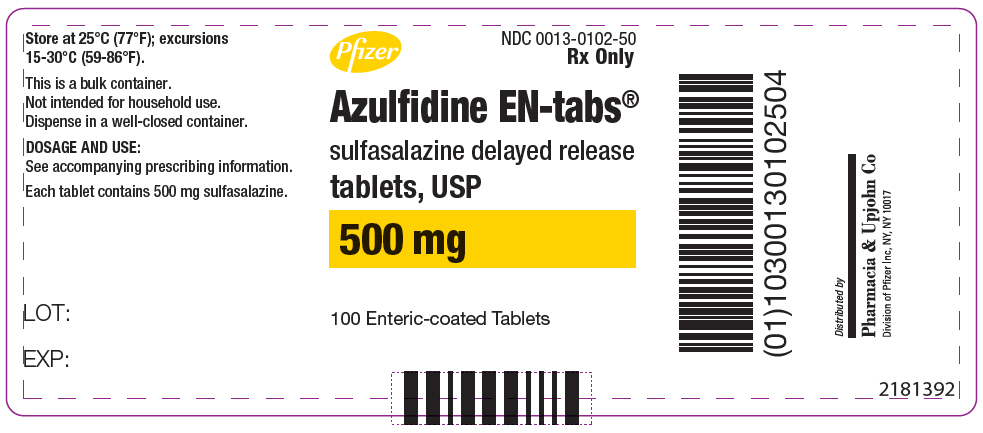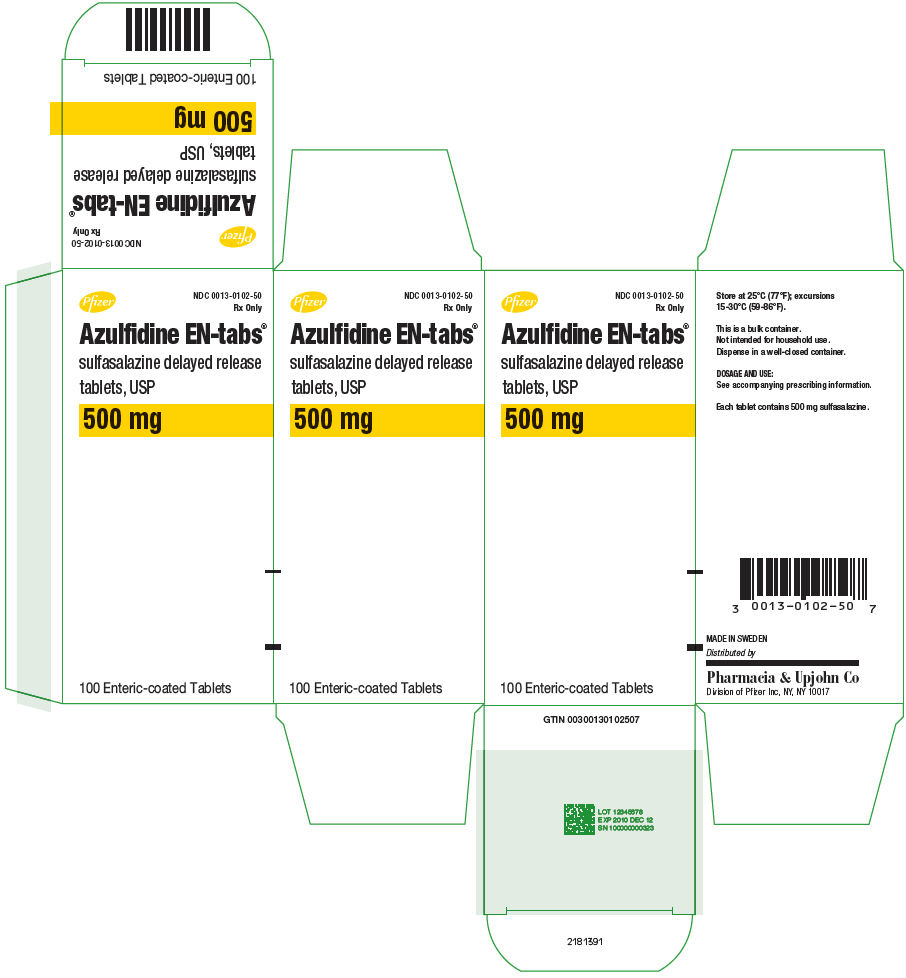 DRUG LABEL: Azulfidine
NDC: 0013-0102 | Form: TABLET, DELAYED RELEASE
Manufacturer: Pfizer Laboratories Div Pfizer Inc
Category: prescription | Type: HUMAN PRESCRIPTION DRUG LABEL
Date: 20251031

ACTIVE INGREDIENTS: SULFASALAZINE 500 mg/1 1
INACTIVE INGREDIENTS: WHITE WAX; CARNAUBA WAX; CELLACEFATE; MAGNESIUM STEARATE; POLYETHYLENE GLYCOL 20000; POVIDONE, UNSPECIFIED; PROPYLENE GLYCOL; GLYCERYL STEARATE SE; SILICON DIOXIDE; STARCH, CORN; TALC

Azulfidine EN-tabs®
sulfasalazine delayed release tablets, USP

Enteric-coated Tablets

DESCRIPTION

AZULFIDINE EN-tabs Tablets contain sulfasalazine, formulated in a delayed release tablet (enteric-coated), 500 mg, for oral administration.

AZULFIDINE EN-tabs Tablets are film coated with cellulose acetate phthalate to retard disintegration of the tablet in the stomach and reduce potential irritation of the gastric mucosa.

Therapeutic Classification: Anti-inflammatory agent and/or immunomodulatory agent.

Chemical Designation: 5-([p-(2-pyridylsulfamoyl)phenyl]azo) salicylic acid.

Chemical Structure:

Molecular Formula: C18H14N4O5S

Inactive ingredients: beeswax (white), carnauba wax, cellacefate, magnesium stearate, polyethylene glycol, povidone, propylene glycol, self-emulsifying glycerol monostearate, silica (colloidal anhydrous), starch (pregelatinized), talc.

CLINICAL PHARMACOLOGY

Pharmacodynamics

The mode of action of sulfasalazine (SSZ) or its metabolites, 5-aminosalicylic acid (5-ASA) and sulfapyridine (SP), may be related to the anti-inflammatory and/or immunomodulatory properties that have been observed in animal and in vitro models, to its affinity for connective tissue, and/or to the relatively high concentration it reaches in serous fluids, the liver and intestinal walls, as demonstrated in autoradiographic studies in animals. In ulcerative colitis, clinical studies utilizing rectal administration of SSZ, SP and 5-ASA have indicated that the major therapeutic action may reside in the 5-ASA moiety. The relative contribution of the parent drug and the major metabolites in rheumatoid arthritis is unknown.

Pharmacokinetics

In vivo studies have indicated that the absolute bioavailability of orally administered SSZ is less than 15% for parent drug. In the intestine, SSZ is metabolized by intestinal bacteria to SP and 5-ASA. Of the two species, SP is relatively well absorbed from the intestine and highly metabolized, while 5-ASA is much less well absorbed.

Absorption

Following oral administration of 1 g of SSZ to 9 healthy males, less than 15% of a dose of SSZ is absorbed as parent drug. Detectable serum concentrations of SSZ have been found in healthy subjects within 90 minutes after the ingestion. Maximum concentrations of SSZ occur between 3 and 12 hours post-ingestion, with the mean peak concentration (6 µg/mL) occurring at 6 hours.

In comparison, peak plasma levels of both SP and 5-ASA occur approximately 10 hours after dosing. This longer time to peak is indicative of gastrointestinal transit to the lower intestine, where bacteria-mediated metabolism occurs. SP apparently is well absorbed from the colon, with an estimated bioavailability of 60%. In this same study, 5-ASA is much less well absorbed from the gastrointestinal tract, with an estimated bioavailability of from 10% to 30%.

Distribution

Following intravenous injection, the calculated volume of distribution (Vdss) for SSZ was 7.5 ± 1.6 L. SSZ is highly bound to albumin (>99.3%), while SP is only about 70% bound to albumin. Acetylsulfapyridine (AcSP), the principal metabolite of SP, is approximately 90% bound to plasma proteins.

Metabolism

As mentioned above, SSZ is metabolized by intestinal bacteria to SP and 5-ASA. Approximately 15% of a dose of SSZ is absorbed as parent and is metabolized to some extent in the liver to the same two species. The observed plasma half-life for intravenous sulfasalazine is 7.6 ± 3.4 hrs. The primary route of metabolism of SP is via acetylation to form AcSP. The rate of metabolism of SP to AcSP is dependent upon acetylator phenotype. In fast acetylators, the mean plasma half-life of SP is 10.4 hrs, while in slow acetylators it is 14.8 hrs. SP can also be metabolized to 5-hydroxy-sulfapyridine (SPOH) and N-acetyl-5-hydroxy-sulfapyridine. 5-ASA is primarily metabolized in both the liver and intestine to N-acetyl-5-aminosalicylic acid via a nonacetylation phenotype dependent route. Due to low plasma levels produced by 5-ASA after oral administration, reliable estimates of plasma half-life are not possible.

Excretion

Absorbed SP and 5-ASA and their metabolites are primarily eliminated in the urine either as free metabolites or as glucuronide conjugates. The majority of 5-ASA stays within the colonic lumen and is excreted as 5-ASA and acetyl-5-ASA with the feces. The calculated clearance of SSZ following intravenous administration was 1 L/hr. Renal clearance was estimated to account for 37% of total clearance.

Special Populations

Elderly

Elderly patients with rheumatoid arthritis showed a prolonged plasma half-life for SSZ, SP, and their metabolites. The clinical impact of this is unknown.

Pediatric

Small studies have been reported in the literature in children down to the age of 4 years with ulcerative colitis and inflammatory bowel disease. In these populations, relative to adults, the pharmacokinetics of SSZ and SP correlated poorly with either age or dose. To date, comparative pharmacokinetic trials have not been conducted to determine whether or not significant pharmacokinetic differences exist between children with juvenile rheumatoid arthritis and adults with rheumatoid arthritis.

Acetylator Status

The metabolism of SP to AcSP is mediated by polymorphic enzymes such that two distinct populations of slow and fast metabolizers exist. Approximately 60% of the Caucasian population can be classified as belonging to the slow acetylator phenotype. These subjects will display a prolonged plasma half-life for SP (14.8 hrs vs. 10.4 hrs) and an accumulation of higher plasma levels of SP than fast acetylators. The clinical implication of this is unclear; however, in a small pharmacokinetic trial where acetylator status was determined, subjects who were slow acetylators of SP showed a higher incidence of adverse events.

Gender

Gender appears not to have an effect on either the rate or the pattern of metabolites of SSZ, SP, or 5-ASA.

INDICATIONS AND USAGE

AZULFIDINE EN-tabs Tablets are indicated:

a) in the treatment of mild to moderate ulcerative colitis, and as adjunctive therapy in severe ulcerative colitis;
b) for the prolongation of the remission period between acute attacks of ulcerative colitis;
c) in the treatment of patients with rheumatoid arthritis who have responded inadequately to salicylates or other nonsteroidal anti-inflammatory drugs (e.g., an insufficient therapeutic response to, or intolerance of, an adequate trial of full doses of one or more nonsteroidal anti-inflammatory drugs); and
d) in the treatment of pediatric patients with polyarticular-course^1 juvenile rheumatoid arthritis who have responded inadequately to salicylates or other nonsteroidal anti-inflammatory drugs.

AZULFIDINE EN-tabs is particularly indicated in patients with ulcerative colitis who cannot take uncoated sulfasalazine tablets because of gastrointestinal intolerance, and in whom there is evidence that this intolerance is not primarily the result of high blood levels of sulfapyridine and its metabolites, e.g., patients experiencing nausea and vomiting with the first few doses of the drug, or patients in whom a reduction in dosage does not alleviate the adverse gastrointestinal effects.

In patients with rheumatoid arthritis or juvenile rheumatoid arthritis, rest and physiotherapy as indicated should be continued. Unlike anti-inflammatory drugs, AZULFIDINE EN-tabs does not produce an immediate response. Concurrent treatment with analgesics and/or nonsteroidal anti-inflammatory drugs is recommended at least until the effect of AZULFIDINE EN-tabs is apparent.

CONTRAINDICATIONS

AZULFIDINE EN-tabs Tablets are contraindicated in:
Hypersensitivity to sulfasalazine, its metabolites, sulfonamides or salicylates,
Patients with intestinal or urinary obstruction,
Patients with porphyria, as the sulfonamides have been reported to precipitate an acute attack.

WARNINGS

Hepatic, Renal, and Hematologic Toxicity or Other Conditions

Only after critical appraisal should AZULFIDINE EN-tabs Tablets be given to patients with hepatic or renal damage or blood dyscrasias. Deaths associated with the administration of sulfasalazine have been reported from hypersensitivity reactions, agranulocytosis, aplastic anemia, other blood dyscrasias, renal and liver damage, irreversible neuromuscular and central nervous system changes, and fibrosing alveolitis. The presence of clinical signs such as sore throat, fever, pallor, purpura, or jaundice may be indications of serious blood disorders or hepatotoxicity. Complete blood counts, as well as urinalysis with careful microscopic examination, should be done frequently in patients receiving AZULFIDINE EN-tabs (see PRECAUTIONS, Laboratory Tests). Discontinue treatment with sulfasalazine while awaiting the results of blood tests. Discontinue AZULFIDINE EN-tabs if renal function deteriorates while on therapy.

Oligospermia and infertility have been observed in men treated with sulfasalazine; however, withdrawal of the drug appears to reverse these effects.

Serious Infections

Serious infections, including fatal sepsis and pneumonia, have been reported. Some infections were associated with agranulocytosis, neutropenia, or myelosuppression. Discontinue AZULFIDINE EN-tabs if a patient develops a serious infection. Closely monitor patients for the development of signs and symptoms of infection during and after treatment with AZULFIDINE EN-tabs. For a patient who develops a new infection during treatment with AZULFIDINE EN-tabs, perform a prompt and complete diagnostic workup for infection and myelosuppression. Caution should be exercised when considering the use of sulfasalazine in patients with a history of recurring or chronic infections or with underlying conditions or concomitant drugs which may predispose patients to infections.

Hypersensitivity Reactions

Severe hypersensitivity reactions may include internal organ involvement, such as hepatitis, nephritis, myocarditis, mononucleosis-like syndrome (i.e., pseudomononucleosis), hematological abnormalities (including hematophagic histiocytosis), and/or pneumonitis including eosinophilic infiltration.

Severe Cutaneous Adverse Reactions

Drug Reactions with Eosinophilia and Systemic Symptoms (DRESS)

Severe, life-threatening, systemic hypersensitivity reactions such as drug reaction with eosinophilia and systemic symptoms (DRESS) have been reported in patients taking sulfasalazine. Early manifestations of hypersensitivity, such as fever or lymphadenopathy, may be present even though rash is not evident. If such signs or symptoms are present, evaluate the patient immediately. Discontinue AZULFIDINE EN-tabs if an alternative etiology for the signs or symptoms cannot be established.

Other severe cutaneous adverse reactions, including exfoliative dermatitis, Stevens-Johnson syndrome (SJS) and toxic epidermal necrolysis (TEN), and acute generalized exanthematous pustulosis (AGEP) have been reported in association with the use of sulfasalazine (see ADVERSE REACTIONS). Severe cutaneous adverse reactions can be serious and are sometimes fatal. Patients are at highest risk for these events early in therapy, with most events occurring within the first month of treatment. Discontinue AZULFIDINE EN-tabs at the first appearance of signs or symptoms of severe cutaneous adverse reactions or other signs of hypersensitivity and consider further evaluation.

PRECAUTIONS

General

AZULFIDINE EN-tabs Tablets should be given with caution to patients with severe allergy or bronchial asthma. Adequate fluid intake must be maintained in order to prevent crystalluria and stone formation. Patients with glucose-6-phosphate dehydrogenase deficiency should be observed closely for signs of hemolytic anemia. This reaction is frequently dose related. If toxic or hypersensitivity reactions occur, AZULFIDINE EN-tabs should be discontinued immediately.

Isolated instances have been reported when AZULFIDINE EN-tabs Tablets have passed undisintegrated. If this is observed, the administration of AZULFIDINE EN-tabs should be discontinued immediately.

Information For Patients

Patients should be informed of the possibility of adverse effects and of the need for careful medical supervision. The occurrence of sore throat, fever, pallor, purpura, or jaundice may indicate a serious blood disorder. Should any of these occur, the patient should seek medical advice.

Patients should be instructed to take AZULFIDINE EN-tabs in evenly divided doses, preferably after meals, and to swallow the tablets whole. Additionally, patients should be advised that sulfasalazine may produce an orange-yellow discoloration of the urine or skin.

Ulcerative Colitis

Patients with ulcerative colitis should be made aware that ulcerative colitis rarely remits completely, and that the risk of relapse can be substantially reduced by continued administration of AZULFIDINE EN-tabs at a maintenance dosage.

Rheumatoid Arthritis

Rheumatoid arthritis rarely remits. Therefore, continued administration of AZULFIDINE EN-tabs is indicated. Patients requiring sulfasalazine should follow up with their physicians to determine the need for continued administration.

Laboratory Tests

Complete blood counts, including differential white cell count, and liver function tests, should be performed before starting AZULFIDINE EN-tabs and every second week during the first three months of therapy. During the second three months, the same tests should be done once monthly and thereafter once every three months, and as clinically indicated. Urinalysis and an assessment of renal function should also be done periodically during treatment with AZULFIDINE EN-tabs.

The determination of serum sulfapyridine levels may be useful since concentrations greater than 50 µg/mL appear to be associated with an increased incidence of adverse reactions.

Drug Interactions

Reduced absorption of folic acid and digoxin have been reported when those agents were administered concomitantly with sulfasalazine.

When daily doses of sulfasalazine 2 g and weekly doses of methotrexate 7.5 mg were coadministered to 15 rheumatoid arthritis patients in a drug-drug interaction study, the pharmacokinetic disposition of the drugs was not altered.

Daily doses of sulfasalazine 2 g (maximum 3 g) and weekly doses of methotrexate 7.5 mg (maximum 15 mg) were administered alone or in combination to 310 rheumatoid arthritis patients in two controlled 52-week clinical studies. The overall toxicity profile of the combination revealed an increased incidence of gastrointestinal adverse events, especially nausea, when compared to the incidence associated with either drug administered alone.

Drug/Laboratory Test Interactions

Several reports of possible interference with measurements, by liquid chromatography, of urinary normetanephrine causing a false-positive test result have been observed in patients exposed to sulfasalazine or its metabolite, mesalamine/mesalazine.

Sulfasalazine or its metabolite, sulfapyridine, may interfere with ultraviolet absorbance, particularly at 340 nm, and may cause interference with some laboratory assays that use nicotinamide adenine dinucleotide [NAD(H)] or nicotinamide adenine dinucleotide phosphate [NADP(H)] to measure ultraviolet absorbance around that wavelength. Examples of such assays may include alanine aminotransferase (ALT), aspartate aminotransferase (AST), creatine kinase-muscle/brain (CK-MB), ammonia, thyroxine or glucose. Erroneous laboratory results may be observed in patients receiving higher than recommended dosages of sulfasalazine.

Carcinogenesis, Mutagenesis, Impairment of Fertility

Two year oral carcinogenicity studies were conducted in male and female F344/N rats and B6C3F1 mice. Sulfasalazine was tested at 84 (496 mg/m^2), 168 (991 mg/m^2) and 337.5 (1991 mg/m^2) mg/kg/day doses in rats. A statistically significant increase in the incidence of urinary bladder transitional cell papillomas was observed in male rats. In female rats, two (4%) of the 337.5 mg/kg rats had transitional cell papilloma of the kidney. The increased incidence of neoplasms in the urinary bladder and kidney of rats was also associated with an increase in the renal calculi formation and hyperplasia of transitional cell epithelium. For the mouse study, sulfasalazine was tested at 675 (2025 mg/m^2), 1350 (4050 mg/m^2) and 2700 (8100 mg/m^2) mg/kg/day. The incidence of hepatocellular adenoma or carcinoma in male and female mice was significantly greater than the control at all doses tested.

Sulfasalazine did not show mutagenicity in the bacterial reverse mutation assay (Ames test) or in the L51784 mouse lymphoma cell assay at the HGPRT gene. However, sulfasalazine showed equivocal mutagenic response in the micronucleus assay of mouse and rat bone marrow and mouse peripheral RBC and in the sister chromatid exchange, chromosomal aberration, and micronucleus assays in lymphocytes obtained from humans.

Impairment of male fertility was observed in reproductive studies performed in rats at a dose of 800 mg/kg/day (4800 mg/m^2). Oligospermia and infertility have been described in men treated with sulfasalazine. Withdrawal of the drug appears to reverse these effects.

Pregnancy

TERATOGENIC EFFECTS

There are no adequate and well-controlled studies of sulfasalazine in pregnant women. Reproduction studies have been performed in rats and rabbits at doses up to 6 times the human maintenance dose of 2 g/day based on body surface area and have revealed no evidence of impaired female fertility or harm to the fetus due to sulfasalazine. Because animal reproduction studies are not always predictive of human response, this drug should be used during pregnancy only if clearly needed.

There have been case reports of neural tube defects (NTDs) in infants born to mothers who were exposed to sulfasalazine during pregnancy, but the role of sulfasalazine in these defects has not been established. However, oral sulfasalazine inhibits the absorption and metabolism of folic acid which may interfere with folic acid supplementation (see Drug Interactions) and diminish the effect of periconceptional folic acid supplementation that has been shown to decrease the risk of NTDs.

A national survey evaluated the outcome of pregnancies associated with inflammatory bowel disease (IBD). In 186 pregnancies in women treated with sulfasalazine alone or sulfasalazine and concomitant steroid therapy, the incidence of fetal morbidity and mortality was comparable both to that of 245 untreated IBD pregnancies, and to pregnancies in the general population.^2

A study of 1455 pregnancies associated with exposure to sulfonamides including sulfasalazine, indicated that this group of drugs did not appear to be associated with fetal malformation.^3 A review of the medical literature covering 1155 pregnancies in women with ulcerative colitis suggested that the outcome was similar to that expected in the general population.^4

No clinical studies have been performed to evaluate the effect of sulfasalazine on the growth development and functional maturation of children whose mothers received the drug during pregnancy.

Clinical Considerations

Sulfasalazine and its metabolite, sulfapyridine, pass through the placenta. Sulfasalazine and its metabolite are also present in human milk. In the newborn, sulfonamides compete with bilirubin for binding sites on the plasma proteins and may cause kernicterus. Although sulfapyridine has been shown to have poor bilirubin-displacing capacity, monitor the newborn for the potential for kernicterus.

A case of agranulocytosis has been reported in an infant whose mother was taking both sulfasalazine and prednisone throughout pregnancy.

Nursing Mothers

Sulfonamides, including sulfasalazine, are present in human milk (see Pregnancy, Clinical Considerations). Insignificant amounts of sulfasalazine have been found in milk, whereas levels of the active metabolite sulfapyridine in milk are about 30 to 60 percent of those in the maternal serum. Caution should be exercised when AZULFIDINE EN-tabs is administered to a nursing mother.

There are reports with limited data of bloody stools or diarrhea in human milk fed infants of mothers taking sulfasalazine. In cases where the outcome was reported, bloody stools or diarrhea resolved in the infant after discontinuation of sulfasalazine in the mother or discontinuation of breastfeeding. Due to limited data, a causal relationship between sulfasalazine exposure and bloody stools or diarrhea cannot be confirmed or denied. Monitor human milk fed infants of mothers taking sulfasalazine for signs and symptoms of diarrhea and/or bloody stools.

Pediatric Use

The safety and effectiveness of AZULFIDINE EN-tabs in pediatric patients below the age of 2 years with ulcerative colitis have not been established.

The safety and effectiveness of AZULFIDINE EN-tabs for the treatment of the signs and symptoms of polyarticular-course juvenile rheumatoid arthritis in pediatric patients aged 6–16 years is supported by evidence from adequate and well-controlled studies in adult rheumatoid arthritis patients. The extrapolation from adults with rheumatoid arthritis to children with polyarticular-course juvenile rheumatoid arthritis is based on similarities in disease and response to therapy between these two patient populations. Published studies support the extrapolation of safety and effectiveness for sulfasalazine to polyarticular-course juvenile rheumatoid arthritis^1,5 (see ADVERSE REACTIONS).

It has been reported that the frequency of adverse events in patients with systemic-course of juvenile arthritis is high.^6 Use in children with systemic-course juvenile rheumatoid arthritis has frequently resulted in a serum sickness-like reaction.^5 This reaction is often severe and presents as fever, nausea, vomiting, headache, rash, and abnormal liver function tests. Treatment of systemic-course juvenile rheumatoid arthritis with sulfasalazine is not recommended.

ADVERSE REACTIONS

The most common adverse reactions associated with sulfasalazine in ulcerative colitis are anorexia, headache, nausea, vomiting, gastric distress, and apparently reversible oligospermia. These occur in about one-third of the patients. Less frequent adverse reactions are pruritus, urticaria, rash, fever, Heinz body anemia, hemolytic anemia, and cyanosis, which may occur at a frequency of 1 in 30 patients or less. Experience suggests that with a daily dose of 4 g or more, or total serum sulfapyridine levels above 50 µg/mL, the incidence of adverse reactions tends to increase.

Similar adverse reactions are associated with sulfasalazine use in adult rheumatoid arthritis, although there was a greater incidence of some reactions. In rheumatoid arthritis studies, the following common adverse reactions were noted: nausea (19%), dyspepsia (13%), rash (13%), headache (9%), abdominal pain (8%), vomiting (8%), fever (5%), dizziness (4%), stomatitis (4%), pruritis (4%), abnormal liver function tests (4%), leukopenia (3%), and thrombocytopenia (1%). One report^7 showed a 10% rate of immunoglobulin suppression, which was slowly reversible and rarely accompanied by clinical findings.

In general, the adverse reactions in juvenile rheumatoid arthritis patients are similar to those seen in patients with adult rheumatoid arthritis except for a high frequency of serum sickness-like syndrome in systemic-course juvenile rheumatoid arthritis (see PRECAUTIONS, Pediatric Use). One clinical trial showed an approximate 10% rate of immunoglobulin suppression.^1

Although the listing which follows includes a few adverse reactions which have not been reported with this specific drug, the pharmacological similarities among the sulfonamides require that each of these reactions be considered when AZULFIDINE EN-tabs is administered.

Less common or rare adverse reactions include:

Blood dyscrasias: aplastic anemia, agranulocytosis, megaloblastic (macrocytic) anemia, purpura, hypoprothrombinemia, methemoglobinemia, congenital neutropenia, and myelodysplastic syndrome.

Hypersensitivity reactions: erythema multiforme, epidermal necrolysis (SJS/TEN) with corneal damage, exfoliative dermatitis, DRESS, anaphylaxis, serum sickness syndrome, interstitial lung disease, pneumonitis with or without eosinophilia, vasculitis, fibrosing alveolitis, pleurisy/pleuritis, pericarditis with or without tamponade, allergic myocarditis, polyarteritis nodosa, lupus erythematosus-like syndrome, hepatitis and hepatic necrosis with or without immune complexes, fulminant hepatitis, sometimes leading to liver transplantation, parapsoriasis varioliformis acuta (Mucha-Haberman syndrome), rhabdomyolysis, photosensitization, arthralgia, periorbital edema, conjunctival and scleral injection and alopecia.

Gastrointestinal reactions: hepatitis, hepatic failure, pancreatitis, bloody diarrhea, impaired folic acid absorption, impaired digoxin absorption, stomatitis, diarrhea, abdominal pains, and neutropenic enterocolitis.

Central Nervous System reactions: transverse myelitis, convulsions, meningitis, transient lesions of the posterior spinal column, cauda equina syndrome, Guillain-Barre syndrome, peripheral neuropathy, mental depression, vertigo, hearing loss, insomnia, ataxia, hallucinations, tinnitus, and drowsiness.

Renal reactions: toxic nephrosis with oliguria and anuria, nephritis, nephrotic syndrome, urinary tract infections, hematuria, crystalluria, proteinuria, and hemolytic-uremic syndrome.

Other reactions: urine discoloration and skin discoloration.

The sulfonamides bear certain chemical similarities to some goitrogens, diuretics (acetazolamide and the thiazides), and oral hypoglycemic agents. Goiter production, diuresis and hypoglycemia have occurred rarely in patients receiving sulfonamides.

Cross-sensitivity may exist with these agents. Rats appear to be especially susceptible to the goitrogenic effects of sulfonamides and long-term administration has produced thyroid malignancies in this species.

Postmarketing Reports

The following events have been identified during post-approval use of products which contain (or are metabolized to) mesalamine in clinical practice. Because they are reported voluntarily from a population of unknown size, estimates of frequency cannot be made. These events have been chosen for inclusion due to a combination of seriousness, frequency of reporting, or potential causal connection to mesalamine:

Blood dyscrasias: pseudomononucleosis

Cardiac disorders: myocarditis

Hepatobiliary disorders: reports of hepatotoxicity, including elevated liver function tests (SGOT/AST, SGPT/ALT, GGT, LDH, alkaline phosphatase, bilirubin), jaundice, cholestatic jaundice, cirrhosis, hepatitis cholestatic, cholestasis and possible hepatocellular damage including liver necrosis and liver failure. Some of these cases were fatal. One case of Kawasaki-like syndrome, which included hepatic function changes, was also reported.

Immune system disorders: anaphylaxis

Metabolism and nutrition system disorders: folate deficiency

Renal and urinary disorders: nephrolithiasis

Respiratory, thoracic and mediastinal disorders: oropharyngeal pain

Skin and subcutaneous tissue disorders: angioedema, purpura, SJS/TEN, DRESS, and AGEP

Vascular disorders: pallor

DRUG ABUSE AND DEPENDENCE

None reported.

OVERDOSAGE

There is evidence that the incidence and severity of toxicity following overdosage is directly related to the total serum sulfapyridine concentration. Symptoms of overdosage may include nausea, vomiting, gastric distress and abdominal pains. In more advanced cases, central nervous system symptoms such as drowsiness, convulsions, etc., may be observed. Serum sulfapyridine concentrations may be used to monitor the progress of recovery from overdosage.

There are no documented reports of deaths due to ingestion of large single doses of sulfasalazine. It has not been possible to determine the LD50 in laboratory animals such as mice, since the highest oral daily dose of sulfasalazine which can be given (12 g/kg) is not lethal. Doses of regular sulfasalazine tablets of 16 g per day have been given to patients without mortality.

Instructions for Overdosage

Gastric lavage or emesis plus catharsis as indicated. Alkalinize urine. If kidney function is normal, force fluids. If anuria is present, restrict fluids and salt, and treat appropriately. Catheterization of the ureters may be indicated for complete renal blockage by crystals. The low molecular weight of sulfasalazine and its metabolites may facilitate their removal by dialysis.

DOSAGE AND ADMINISTRATION

The dosage of AZULFIDINE EN-tabs Tablets should be adjusted to each individual's response and tolerance.

Patients should be instructed to take AZULFIDINE EN-tabs in evenly divided doses, preferably after meals, and to swallow the tablets whole.

Ulcerative Colitis

Initial Therapy

Adults: 3 to 4 g daily in evenly divided doses with dosage intervals not exceeding eight hours. It may be advisable to initiate therapy with a lower dosage, e.g., 1 to 2 g daily, to reduce possible gastrointestinal intolerance. If daily doses exceeding 4 g are required to achieve the desired therapeutic effect, the increased risk of toxicity should be kept in mind.

Children, six years of age and older: 40 to 60 mg/kg of body weight in each 24-hour period, divided into 3 to 6 doses.

Maintenance Therapy

Adults: 2 g daily.

Children, six years of age and older: 30 mg/kg of body weight in each 24-hour period, divided into 4 doses. The response of acute ulcerative colitis to AZULFIDINE EN-tabs can be evaluated by clinical criteria, including the presence of fever, weight changes, and degree and frequency of diarrhea and bleeding, as well as by sigmoidoscopy and the evaluation of biopsy samples. It is often necessary to continue medication even when clinical symptoms, including diarrhea, have been controlled. When endoscopic examination confirms satisfactory improvement, dosage of AZULFIDINE EN-tabs should be reduced to a maintenance level. If diarrhea recurs, dosage should be increased to previously effective levels.

AZULFIDINE EN-tabs is particularly indicated in patients who cannot take uncoated sulfasalazine tablets because of gastrointestinal intolerance (e.g., anorexia, nausea). If symptoms of gastric intolerance (anorexia, nausea, vomiting, etc.) occur after the first few doses of AZULFIDINE EN-tabs, they are probably due to increased serum levels of total sulfapyridine, and may be alleviated by halving the daily dose of AZULFIDINE EN-tabs and subsequently increasing it gradually over several days. If gastric intolerance continues, the drug should be stopped for 5 to 7 days, then reintroduced at a lower daily dose.

Adult Rheumatoid Arthritis

2 g daily in two evenly divided doses. It is advisable to initiate therapy with a lower dosage of AZULFIDINE EN-tabs, e.g., 0.5 to 1.0 g daily, to reduce possible gastrointestinal intolerance. A suggested dosing schedule is given below.

In rheumatoid arthritis, the effect of AZULFIDINE EN-tabs can be assessed by the degree of improvement in the number and extent of actively inflamed joints. A therapeutic response has been observed as early as 4 weeks after starting treatment with AZULFIDINE EN-tabs, but treatment for 12 weeks may be required in some patients before clinical benefit is noted. Consideration can be given to increasing the daily dose of AZULFIDINE EN-tabs to 3 g if the clinical response after 12 weeks is inadequate. Careful monitoring is recommended for doses over 2 g per day.

Suggested Dosing Schedule for Adult Rheumatoid Arthritis:

Week of | Number of AZULFIDINE EN-tabs Tablets
Treatment | Morning | Evening
1 | - | One
2 | One | One
3 | One | Two
4 | Two | Two

Juvenile Rheumatoid Arthritis - polyarticular course

Children, six years of age and older: 30 to 50 mg/kg of body weight daily in two evenly divided doses. Typically, the maximum dose is 2 g per day. To reduce possible gastrointestinal intolerance, begin with a quarter to a third of the planned maintenance dose and increase weekly until reaching the maintenance dose at one month.

Some patients may be sensitive to treatment with sulfasalazine. Various desensitization-like regimens have been reported to be effective in 34 of 53 patients,^8 7 of 8 patients,^9 and 19 of 20 patients.^10 These regimens suggest starting with a total daily dose of 50 to 250 mg sulfasalazine initially, and doubling it every 4 to 7 days until the desired therapeutic level is achieved. If the symptoms of sensitivity recur, AZULFIDINE EN-tabs should be discontinued. Desensitization should not be attempted in patients who have a history of agranulocytosis, or who have experienced an anaphylactoid reaction while previously receiving sulfasalazine.

HOW SUPPLIED

AZULFIDINE EN-tabs Tablets, 500 mg, are elliptical, gold-colored, film enteric-coated tablets, monogrammed "102" on one side and "KPh" on the other. They are available in the following package sizes:

Bottle of 100 (with carton) | NDC 0013-0102-50
Bottle of 100 | NDC 0013-0102-01
Bottle of 300 (with carton) | NDC 0013-0102-60
Bottle of 300 | NDC 0013-0102-20

Storage

Store at 25°C (77°F); excursions permitted to 15–30°C (59–86°F) [see USP Controlled Room Temperature].

REFERENCES

1. van Rossum MAJ, et al. Sulfasalazine in the treatment of juvenile chronic arthritis: a randomized, double-blind, placebo-controlled, multicenter study. Arth Rheum 1998;41:808–816.
2. Mogadam M, et al. Pregnancy in inflammatory bowel disease: effect of sulfasalazine and corticosteroids on fetal outcome. Gastroenterology 1981;80:726.
3. Kaufman DW, editor. Birth defects and drugs during pregnancy. Littleton, MA: Publishing Sciences Group, Inc., 1977:296–313.
4. Jarnerot G. Fertility, sterility and pregnancy in chronic inflammatory bowel disease. Scand J Gastroenterol 1982;17:1–4.
5. Imundo LF, Jacobs JC. Sulfasalazine therapy for juvenile rheumatoid arthritis. J Rheumatol 1996;23:360–366.
6. Hertzberger-ten Cate R, Cats A. Toxicity of sulfasalazine in systemic juvenile chronic arthritis. Clin Exp Rheumatol 1991;9:85–8.
7. Farr M, et al. Immunodeficiencies associated with sulphasalazine therapy in inflammatory arthritis. British Jnl Rheum 1991;30:413–417.
8. Korelitz B, et al. Desensitization to sulfasalazine in allergic patients with IBD: an important therapeutic modality. Gastroenterology 1982;82:1104.
9. Holdworth CG. Sulphasalazine desensitization. Br Med J 1981;282:110.
10. Taffet SL, Das KM. Desensitization of patients with inflammatory bowel disease to sulfasalazine. Am J Med 1982;73:520–4.

This product's label may have been updated. For current full prescribing information, please visit www.pfizer.com.

LAB-0237-18.0

Revised: 4/2025

PRINCIPAL DISPLAY PANEL - 500 mg Tablet Bottle Label

Pfizer

NDC 0013-0102-01
Rx Only

Azulfidine EN-tabs®

sulfasalazine delayed release
tablets, USP

500 mg

100 Enteric-coated Tablets

PRINCIPAL DISPLAY PANEL - 500 mg Tablet Bottle Label - NDC 0013-0102-50

Pfizer

NDC 0013-0102-50
Rx Only

Azulfidine EN-tabs®

sulfasalazine delayed release
tablets, USP

500 mg

100 Enteric-coated Tablets

PRINCIPAL DISPLAY PANEL - 500 mg Tablet Bottle Carton - NDC 0013-0102-50

Pfizer

NDC 0013-0102-50
Rx Only

Azulfidine EN-tabs®

sulfasalazine delayed release
tablets, USP

500 mg

100 Enteric-coated Tablets